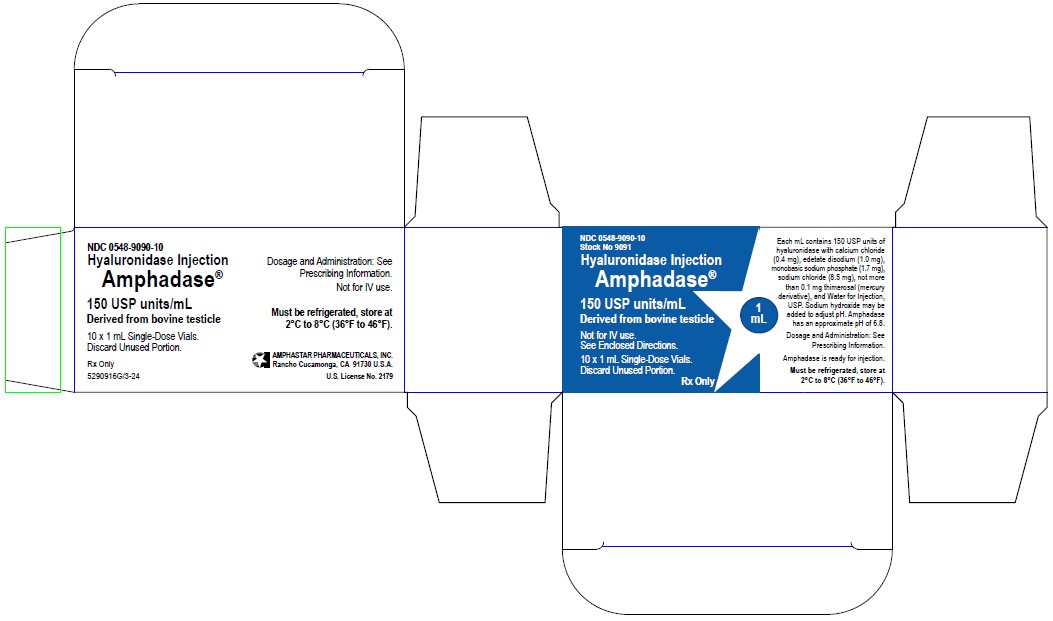 DRUG LABEL: 
                  AMPHADASE
                  
                
NDC: 0548-9090 | Form: INJECTION
Manufacturer: Amphastar Pharmaceuticals, Inc. 
Category: prescription | Type: HUMAN PRESCRIPTION DRUG LABEL
Date: 20240201

ACTIVE INGREDIENTS: hyaluronidase  150 [USP'U]/1 mL
INACTIVE INGREDIENTS: sodium chloride  8.5  mg/1 mL; edetate disodium  1 mg/1 mL; calcium chloride 0.4 mg/1 mL; SODIUM PHOSPHATE, MONOBASIC; thimerosal

HIGHLIGHTS OF PRESCRIBING INFORMATION

These highlights do not include all the information needed to use AMPHADASE® safely and effectively. See full prescribing information for AMPHADASE®.
AMPHADASE® (hyaluronidase injection), for infiltration use, for interstitial use, for intramuscular use, for peribulbar use, for retrobulbar use, for soft tissue use, or for subcutaneous use
Initial U.S. Approval: 2005

1 INDICATIONS AND USAGE

Amphadase® is an endoglycosidase indicated as an adjuvant:
• in subcutaneous fluid administration for achieving hydration (1.1)
• to increase absorption and dispersion of other injected drugs (1.2)
• in subcutaneous urography for improving resorption of radiopaque agents (1.3)

2 DOSAGE AND ADMINISTRATION

• Subcutaneous Fluid Administration: Insert needle with aseptic precautions. With tip lying free and movable between skin and muscle, begin clysis; fluid should start in readily without pain or lump. Then inject Amphadase® (hyaluronidase injection) into rubber tubing close to needle. (2.1)
• Absorption and Dispersion of Injected Drugs: Absorption and dispersion of other injected drugs may be enhanced by adding 50 units to 300 units, most typically 150 units hyaluronidase, to the injection solution. (2.2)
• Subcutaneous Urography: The subcutaneous route of administration of urographic contrast media is indicated when intravenous administration cannot be successfully accomplished, particularly in infants and small children. With the patient prone, 75 units of Amphadase® (hyaluronidase injection) is injected subcutaneously over each scapula, followed by injection of the contrast medium at the same sites. (2.3)

3 DOSAGE FORMS AND STRENGTHS

Injection: 150 USP units/mL in a single-dose vial (3)

4 CONTRAINDICATIONS

Hypersensitivity (4.1)

5 WARNINGS AND PRECAUTIONS

• Spread of Localized Infection (5.1)
• Ocular Damage (5.2)
• Enzyme Inactivation with Intravenous Administration (5.3)

6 ADVERSE REACTIONS

Allergic and anaphylactic-like reactions have been reported, rarely (6)

To report SUSPECTED ADVERSE REACTIONS, contact Amphastar Pharmaceuticals, Inc. at 1-800-423-4136 or FDA at 1-800-FDA-1088 or www.fda.gov/medwatch.

7 DRUG INTERACTIONS

• Furosemide, the benzodiazepines and phenytoin are incompatible with hyaluronidase (7.1)
• Hyaluronidase should not be used to enhance the absorption and dispersion of dopamine and/or alpha agonist drugs (7.2)
• Local anesthetics: Hyaluronidase hastens onset and shortens duration of effect, increases incidence of systemic reactions (7.3)
• Large doses of salicylates, cortisone, adrenocorticotropic hormone (ACTH), estrogens or antihistamines may require larger amounts of hyaluronidase for equivalent dispersing effect (7.4)

8 USE IN SPECIFIC POPULATIONS

Pediatric Use: The dosage of subcutaneous fluids administered is dependent upon the age, weight, and clinical condition of the patient. For premature infants or during the neonatal period, the daily dosage should not exceed 25 mL/kg of body weight, and the rate of administration should not be greater than 2 mL per minute. Special care must be taken in pediatric patients to avoid over hydration by controlling the rate and total volume of the infusion. (2.1, 8.4)

FULL PRESCRIBING INFORMATION

1 INDICATIONS AND USAGE

1.1 Subcutaneous Fluid Administration

Amphadase® is indicated as an adjuvant in subcutaneous fluid administration for achieving hydration.

1.2 Dispersion and Absorption of Injected Drugs

Amphadase® is indicated as an adjuvant to increase the dispersion and absorption of other injected drugs.

1.3 Subcutaneous Urography

Amphadase® is indicated as an adjunct in subcutaneous urography for improving resorption of radiopaque agents.

2 DOSAGE AND ADMINISTRATION

Parenteral drug products should be inspected visually for particulate matter and discoloration prior to administration, whenever solution and container permit.

2.1 Subcutaneous Fluid Administration (Hypodermoclysis)

Insert needle with aseptic precautions. With tip lying free and movable between skin and muscle, begin clysis; fluid should start in readily without pain or lump. Then inject Amphadase® (hyaluronidase injection) into rubber tubing close to needle.

An alternate method is to inject Amphadase® under skin prior to clysis. 150 units will facilitate absorption of 1,000 mL or more of solution. As with all parenteral fluid therapy, observe effect closely, with same precautions for restoring fluid and electrolyte balance as in intravenous injections. The dose, the rate of injection, and the type of solution (saline, glucose, Ringer’s, etc.) must be adjusted carefully to the individual patient. When solutions devoid of inorganic electrolytes are given by hypodermoclysis, hypovolemia may occur. This may be prevented by using solutions containing adequate amounts of inorganic electrolytes and/or controlling the volume and speed of administration.

Amphadase® may be added to small volumes of solution (up to 200 mL), such as small clysis for infants or solutions of drugs for subcutaneous injection. For infants and children less than 3 years old, the volume of a single clysis should be limited to 200 mL; and in premature infants or during the neonatal period, the daily dosage should not exceed 25 mL/kg of body weight; the rate of administration should not be greater than 2 mL per minute. For older patients, the rate and volume of administration should not exceed those employed for intravenous infusion.

2.2 Absorption and Dispersion of Injected Drugs

Absorption and dispersion of other injected drugs may be enhanced by adding 50 units to 300 units, most typically 150 units hyaluronidase, to the injection solution.

2.3 Subcutaneous Urography

The subcutaneous route of administration of urographic contrast media is indicated when intravenous administration cannot be successfully accomplished, particularly in infants and small children. With the patient prone, 75 units of Amphadase® (hyaluronidase injection) is injected subcutaneously over each scapula, followed by injection of the contrast medium at the same sites.

3 DOSAGE FORMS AND STRENGTHS

Injection: 150 USP units/mL as a clear and colorless solution single-dose vial.

4 CONTRAINDICATIONS

4.1 Hypersensitivity

Hypersensitivity to hyaluronidase or any other ingredient in the formulation is a contraindication to the use of this product.

5 WARNINGS AND PRECAUTIONS

5.1 Spread of Localized Infection

Hyaluronidase should not be injected into or around an infected or acutely inflamed area because of the danger of spreading a localized infection.
Hyaluronidase should not be used to reduce the swelling of bites or stings.

5.2 Ocular Damage

Hyaluronidase should not be applied directly to the cornea.

5.3 Enzyme Inactivation with Intravenous Administration

Hyaluronidase should not be used for intravenous injections because the enzyme is rapidly inactivated.

6 ADVERSE REACTIONS

The following adverse reactions have been identified during post-approval use of hyaluronidase products. Because these reactions are reported voluntarily from a population of uncertain size, it is not always possible to reliably estimate their frequency or establish a causal relationship to drug exposure. The most frequently reported adverse reactions have been local injection site reactions.

Hyaluronidase has been reported to enhance the adverse reactions associated with co-administered drug products. Edema has been reported most frequently in association with hypodermoclysis.

Allergic reactions (urticaria, angioedema) have been reported in less than 0.1% of patients receiving hyaluronidase. Anaphylactic-like reactions following retrobulbar block or intravenous injections have occurred, rarely.

7 DRUG INTERACTIONS

It is recommended that appropriate references be consulted regarding physical or chemical incompatibilities before adding Amphadase® to a solution containing another drug.

7.1 Incompatibilities

Furosemide, the benzodiazepines and phenytoin have been found to be incompatible with hyaluronidase.

Admixture stability studies have shown that 2% lidocaine with 1:100,000 or 1:200,000 epinephrine is incompatible with hyaluronidase due to the presence of sodium metabisulfite, a common additive in anesthetic products containing epinephrine.

7.2 Drug-Specific Precautions

Hyaluronidase should not be used to enhance the dispersion and absorption of dopamine and/or alpha agonist drugs.

When considering the administration of any other drug with hyaluronidase, it is recommended that appropriate references first be consulted to determine the usual precautions for the use of the other drug; e.g., when epinephrine is injected along with hyaluronidase, the precautions for the use of epinephrine in cardiovascular disease, thyroid disease, diabetes, digital nerve block, ischemia of the fingers and toes etc., should be observed.

7.3 Local Anesthetics

When hyaluronidase is added to a local anesthetic agent, it hastens the onset of analgesia and tends to reduce the swelling caused by local infiltration, but the wider spread of the local anesthetic solution increases its absorption; this shortens its duration of action and tends to increase the incidence of systemic reaction.

7.4 Salicylates, Cortisone, ACTH, Estrogens and Antihistamines

Patients receiving large doses of salicylates, cortisone, , adrenocorticotropic hormone (ACTH), estrogens or antihistamines may require larger amounts of hyaluronidase for equivalent dispersing effect, since these drugs apparently render tissues partly resistant to the action of hyaluronidase.

8 USE IN SPECIFIC POPULATIONS

8.1 Pregnancy

Risk Summary

Human studies of hyaluronidase as an aid to conception and as an aid to delivery have been conducted without reports of maternal or fetal harm. There are no available data on Amphadase® use in pregnant women to evaluate for a drug-associated risk of major birth defects, miscarriage or other adverse maternal or fetal outcomes. Animal reproduction studies have not been conducted with Amphadase®.

The estimated background risk of major birth defects and miscarriage for the indicated population is unknown. However, the background risk in the U.S. general population of major birth defects is 2% to 4%, and of miscarriage is 15% to 20%, of clinically recognized pregnancies.

Clinical Considerations
Hyaluronidase has been used as a component to aid the in vitro fertilization of human eggs. Administration of hyaluronidase during labor was reported to cause no complications: no increase in blood loss or differences in cervical trauma were observed.

8.2 Lactation

Risk Summary
There is no information regarding the presence of Amphadase® in human milk, the effects on breastfed infants, or the effects on milk production to inform risk of Amphadase® to an infant during lactation. The developmental and health benefits of breastfeeding should be considered, along with the mother’s clinical need for Amphadase®, and any potential adverse effects on the breastfed infant from Amphadase®.

8.4 Pediatric Use

The safety and effectiveness of Amphadase® have been established in pediatric patients. Use of Amphadase® in these patients is supported by evidence from adequate and well-controlled studies. Clinical hydration requirements for children can be achieved through administration of subcutaneous fluids facilitated with Amphadase®.

The dosage of subcutaneous fluids administered is dependent upon the age, weight, and clinical condition of the patient as well as laboratory determinations. The potential for chemical or physical incompatibilities should be kept in mind [see Drug Interactions (7)].

The rate and volume of subcutaneous fluid administration should not exceed those employed for intravenous infusion. For premature infants or during the neonatal period, the daily dosage should not exceed 25 mL/kg of body weight, and the rate of administration should not be greater than 2 mL per minute.

During subcutaneous fluid administration, special care must be taken in pediatric patients to avoid over hydration by controlling the rate and total volume of the infusion [see Dosage and Administration (2.1)].

8.5 Geriatric Use

No overall differences in safety or effectiveness have been observed between elderly and younger adult patients.

11 DESCRIPTION

Hyaluronidase is an endoglycosidase. It is a preparation of purified bovine testicular hyaluronidase, a protein enzyme. Hyaluronidase is composed of two major glycosylated forms, α and β. The exact chemical structure of this enzyme is unknown.

Amphadase® (hyaluronidase injection) is supplied as a sterile, clear and colorless, ready for use 1 mL solution in a single-dose vial for infiltration use, for interstitial use, for intramuscular use, for peribulbar use, for soft tissue use, or for subcutaneous use. Each mL contains 150 USP units of hyaluronidase with calcium chloride (0.4 mg), edetate disodium (1.0 mg), monobasic sodium phosphate (1.7 mg), sodium chloride (8.5 mg), not more than 0.1 mg thimerosal (mercury derivative), and Water for Injection, USP. Sodium hydroxide may be added to adjust pH.

Amphadase® has an approximate pH of 6.8 and an osmolality of 295 to 355 mOsm.

12 CLINICAL PHARMACOLOGY

12.1 Mechanism of Action

Hyaluronidase is a dispersion agent, which modifies the permeability of connective tissue through the hydrolysis of hyaluronic acid, a polysaccharide found in the intercellular ground substance of connective tissue, and of certain specialized tissues, such as the umbilical cord and vitreous humor. Hyaluronic acid is also present in the capsules of type A and C hemolytic streptococci.

Hyaluronidase hydrolyzes hyaluronic acid by splitting the glucosaminidic bond between C1 of an N-acetylglucosamine moiety and C4 of a glucuronic acid moiety. This temporarily decreases the viscosity of the cellular cement and promotes dispersion of injected fluids or of localized transudates or exudates, thus facilitating their absorption.

Hyaluronidase cleaves glycosidic bonds of hyaluronic acid and, to a variable degree, some other acid mucopolysaccharides of the connective tissue. The activity is measured in vitro by monitoring the decrease in the amount of an insoluble serum albumin-hyaluronic acid complex as the enzyme cleaves the hyaluronic acid component.

12.2 Pharmacodynamics

In the absence of hyaluronidase, material injected subcutaneously disperses very slowly.

Hyaluronidase facilitates dispersion, provided local interstitial pressure is adequate to furnish the necessary mechanical impulse. Such an impulse is normally initiated by injected solutions. The rate and extent of dispersion and absorption is proportionate to the amount of hyaluronidase and the volume of solution.

Results from an experimental study, in humans, on the influence of hyaluronidase in bone repair support the conclusion that this enzyme alone, in the usual clinical dosage, does not deter bone healing.

12.3 Pharmacokinetics

Knowledge of the mechanisms involved in the disappearance of injected hyaluronidase is limited. It is known, however, that the blood of a number of mammalian species brings about the inactivation of hyaluronidase.

Studies have demonstrated that hyaluronidase is antigenic: repeated injections of relatively large amounts of this enzyme may result in the formation of neutralizing antibodies.

13 NONCLINICAL TOXICOLOGY

13.1 Carcinogenesis, Mutagenesis, Impairment of Fertility

Long-term animal studies have not been performed to assess the carcinogenic or mutagenic potential of hyaluronidase. Hyaluronidase is found in most tissues of the body.

Adequate fertility studies have not been conducted in animals, however, it has been reported that testicular degeneration may occur from the production of organ-specific antibodies against this enzyme following repeated injections.

16 HOW SUPPLIED/STORAGE AND HANDLING

Amphadase® (hyaluronidase injection) is supplied as a sterile, clear and colorless solution as 150 USP units of hyaluronidase per mL in a single-dose glass vial with a gray rubber stopper and aluminum flip-off seal. Discard unused portion.

NDC 0548-9090-10, 1 mL single-dose vial, 10 vials/carton.

Store unopened vial in a refrigerator at 2°C to 8°C (36°F to 46° F).

17 PATIENT COUNSELING INFORMATION

Important Precautions Regarding Amphadase®
Instruct patients that Amphadase® is being used to increase the dispersion and absorption of fluids or other injected drugs, as appropriate to the intended use.
Instruct patients that there may be mild local injection site signs and symptoms, such as redness, swelling, itching, or pain localized to the site of injection.

What Patients Should Know About Adverse Reactions
The most frequently reported adverse reactions have been mild local injection site reactions such as redness, swelling, itching, or pain.
Anaphylactic-like reactions, and allergic reactions, such as hives, have been reported rarely in patients receiving hyaluronidases.

Patients Should Inform Their Doctors If Taking Other Medications
You may not receive furosemide, the benzodiazepines, phenytoin, dopamine and/or alpha agonists with Amphadase®. These medications have been found to be incompatible with hyaluronidase.
If you are taking salicylates (e.g., aspirin), steroids (e.g., cortisone or estrogens), or antihistamines your doctor may need to prescribe larger amounts of hyaluronidase for equivalent dispersing effect.

Amphastar Pharmaceuticals, Inc.
Rancho Cucamonga, CA 91730, U.S.A.
Rev. 2/2024

U.S. License No. 2179

6990906T

PRINCIPLE DISPLAY PANEL: Carton: 1mL

NDC 0548-9090-10

Stock No 9091

Hyaluronidase Injection
Amphadase®
150 USP units/mL
Derived from bovine testicle

Not for IV use.
See Enclosed Directions.

10 x 1 mL Single-Dose Vials.
Discard Unused Portion.

Rx Only

1 mL

Each mL contains 150 USP units of hyaluronidase with calcium chloride (0.4 mg),

edetate disodium (1.0 mg), monobasic sodium phosphate (1.7 mg), sodium chloride (8.5 mg),

not more than 0.1 mg thimerosal (mercury derivative), and Water for Injection, USP.

Sodium hydroxide may be added to adjust pH. Amphadase has an approximate pH of 6.8

Dosage and Administration: See Prescribing Information.

Amphadase is ready for injection.

Must be refrigerated, store at 2°C to 8°C (36°F to 46°F).

5290916G/3-24